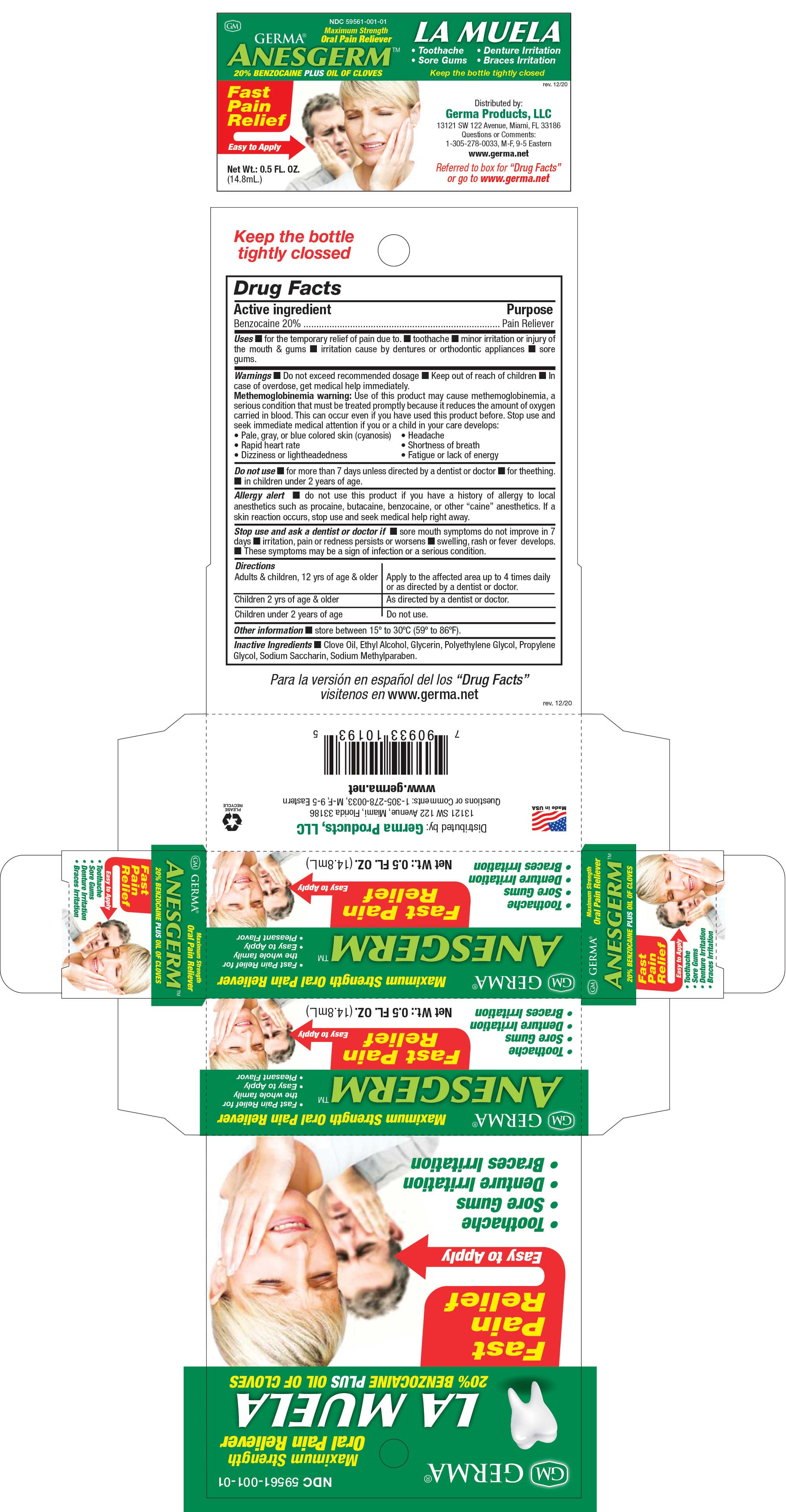 DRUG LABEL: Anesgerm LA MUELA
NDC: 73635-7101 | Form: LIQUID
Manufacturer: Germa Products, LLC
Category: otc | Type: HUMAN OTC DRUG LABEL
Date: 20251010

ACTIVE INGREDIENTS: BENZOCAINE 200 mg/1 mL
INACTIVE INGREDIENTS: PROPYLENE GLYCOL; SACCHARIN SODIUM; GLYCERIN; CLOVE OIL; POLYETHYLENE GLYCOL 100000; ALCOHOL; METHYLPARABEN SODIUM

Anesgerm (La Muella)

Active Ingredient

Benzocaine 20%

Do Not Use if

Do not use ■ for more than 7 days unless directed by a dentist or doctor ■ for teethings. ■ in children under 2 years of age.
Allergy alert ■ do not use this product if you have a history of allergy to local anesthetics such as procaine, butacaine, benzocaine, or other “caine” anesthetics. If a skin reaction occurs, stop use and seek medical help right away.

Stop use and ask a dentist or doctor if ■ sore mouth symptoms do not improve in 7 days ■ irritation, pain or redness persists or worsens ■ swelling, rash or fever develops. ■ These symptoms may be a sign of infection or a serious condition.

Directions

Adults & children, 12 yrs of age & older ■ Apply to the affected area up to 4 times daily or as directed by a dentist or doctor.
Children 2 yrs of age & older ■ As directed by a dentist or doctor.
Children under 2 years of age ■ Do not use.

Purpose

Pain Reliever

Warnings

Do not exceed recommended dosage

Keep out of reach of children

In case of overdose, get medical help immediately.
Methemoglobinemia warning: Use of this product may cause methemoglobinemia, a serious condition that must be treated promptly because it reduces the amount of oxygen carried in blood. This can occur even if you have used this product before. Stop use and seek immediate medical attention if you or a child in your care develops:
Pale, gray, or blue colored skin (cyanosis), Headache, Rapid heart rate, Shortness of breath, Dizziness or lightheadedness, Fatigue or lack of energy.

Do not use:

for more than 7 days unless directed by a dentist or doctor

for teethings in children under 2 years of age.

Allergy alert:

do not use this product if you have a history of allergy to local anesthetics such as procaine, butacaine, benzocaine, or other “caine” anesthetics. If a skin reaction occurs, stop use and seek medical help right away.

Stop use and ask a dentist or doctor if:

sore mouth symptoms do not improve in 7 days.

irritation, pain or redness persists or worsens.

swelling, rash or fever develops.

These symptoms may be a sign of infection or a serious condition.

Other Information

Store between 15º to 30ºC (59º to 86ºF).

Inactive Ingredients

Clove Oil, Ethyl Alcohol, Glycerin, Polyethylene Glycol, Propylene Glycol, Sodium Saccharin, Sodium Methylparaben.

Uses

Uses ■ for the temporary relief of pain due to. ■ toothache ■ minor irritation or injury of the mouth & gums ■ irritation cause by dentures or orthodontic appliances ■ sore gums.

Warning

Warnings: Do not exceed recommended dosage. Keep out of reach of children. In case of overdose, get medical help immediately.
Methemoglobinemia warning: Use of this product may cause methemoglobinemia, a serious condition that must be treated promptly because it reduces the amount of oxygen carried in blood. This can occur even if you have used this product before.